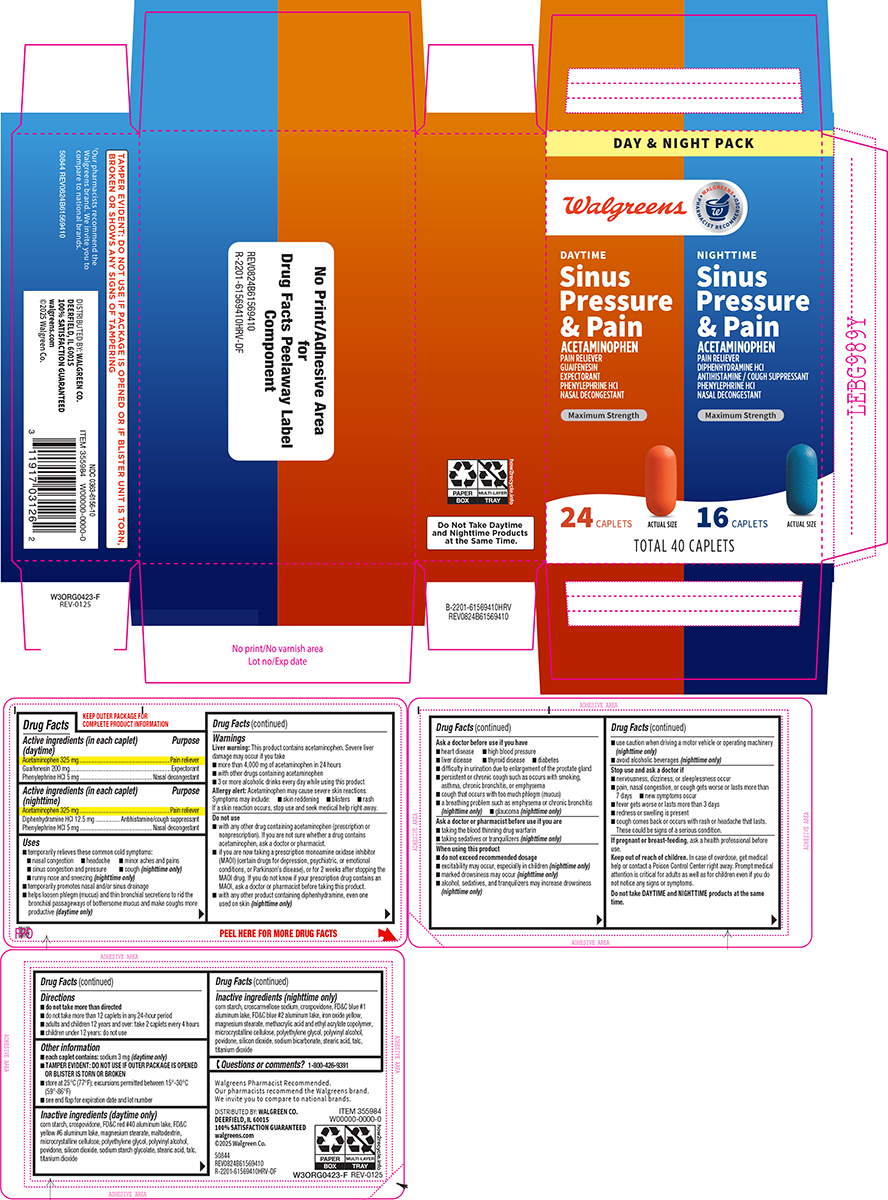 DRUG LABEL: Sinus Pressure and Pain
NDC: 0363-6156 | Form: KIT | Route: ORAL
Manufacturer: Walgreen Company
Category: otc | Type: HUMAN OTC DRUG LABEL
Date: 20251217

ACTIVE INGREDIENTS: ACETAMINOPHEN 325 mg/1 1; GUAIFENESIN 200 mg/1 1; PHENYLEPHRINE HYDROCHLORIDE 5 mg/1 1; ACETAMINOPHEN 325 mg/1 1; DIPHENHYDRAMINE HYDROCHLORIDE 12.5 mg/1 1; PHENYLEPHRINE HYDROCHLORIDE 5 mg/1 1
INACTIVE INGREDIENTS: STARCH, CORN; CROSPOVIDONE, UNSPECIFIED; FD&C RED NO. 40 ALUMINUM LAKE; FD&C YELLOW NO. 6 ALUMINUM LAKE; MAGNESIUM STEARATE; MALTODEXTRIN; MICROCRYSTALLINE CELLULOSE; POLYETHYLENE GLYCOL, UNSPECIFIED; POLYVINYL ALCOHOL, UNSPECIFIED; POVIDONE, UNSPECIFIED; SILICON DIOXIDE; SODIUM STARCH GLYCOLATE TYPE A POTATO; STEARIC ACID; TALC; TITANIUM DIOXIDE; STARCH, CORN; CROSCARMELLOSE SODIUM; CROSPOVIDONE, UNSPECIFIED; FD&C BLUE NO. 1 ALUMINUM LAKE; FD&C BLUE NO. 2 ALUMINUM LAKE; FERRIC OXIDE YELLOW; MAGNESIUM STEARATE; METHACRYLIC ACID AND ETHYL ACRYLATE COPOLYMER; MICROCRYSTALLINE CELLULOSE; POLYETHYLENE GLYCOL, UNSPECIFIED; POLYVINYL ALCOHOL, UNSPECIFIED; POVIDONE, UNSPECIFIED; SILICON DIOXIDE; SODIUM BICARBONATE; STEARIC ACID; TALC; TITANIUM DIOXIDE

Walgreens 44-615694-10-SMH

Active ingredients (in each caplet) (daytime)

Acetaminophen 325 mg
Guaifenesin 200 mg
Phenylephrine HCl 5 mg

Purpose

Pain reliever
Expectorant
Nasal decongestant

Active ingredients (in each caplet) (nighttime)

Acetaminophen 325 mg
Diphenhydramine HCl 12.5 mg
Phenylephrine HCl 5 mg

Purpose

Pain reliever
Antihistamine/cough suppressant
Nasal decongestant

Uses

- temporarily relieves these common cold symptoms:
  - nasal congestion
  - headache
  - minor aches and pains
  - sinus congestion and pressure
  - cough (nighttime only)
  - runny nose and sneezing (nighttime only)
- temporarily promotes nasal and/or sinus drainage
- helps loosen phlegm (mucus) and thin bronchial secretions to rid the bronchial passageways of bothersome mucus and make coughs more productive (daytime only)

Warnings

Liver warning: This product contains acetaminophen. Severe liver damage may occur if you take

- more than 4,000 mg of acetaminophen in 24 hours
- with other drugs containing acetaminophen
- 3 or more alcoholic drinks every day while using this product

Allergy alert: Acetaminophen may cause severe skin reactions. Symptoms may include:

- skin reddening
- blisters
- rash

If a skin reaction occurs, stop use and seek medical help right away.

Do not use

- with any other drug containing acetaminophen (prescription or nonprescription). If you are not sure whether a drug contains acetaminophen, ask a doctor or pharmacist.
- if you are now taking a prescription monoamine oxidase inhibitor (MAOI) (certain drugs for depression, psychiatric, or emotional conditions, or Parkinson’s disease), or for 2 weeks after stopping the MAOI drug. If you do not know if your prescription drug contains an MAOI, ask a doctor or pharmacist before taking this product.
- with any other product containing diphenhydramine, even one used on skin (nighttime only)

Ask a doctor before use if you have

- heart disease
- high blood pressure
- liver disease
- thyroid disease
- diabetes
- difficulty in urination due to enlargement of the prostate gland
- persistent or chronic cough such as occurs with smoking, asthma, chronic bronchitis, or emphysema
- cough that occurs with too much phlegm (mucus)
- a breathing problem such as emphysema or chronic bronchitis (nighttime only)
- glaucoma (nighttime only)

Ask a doctor or pharmacist before use if you are

- taking the blood thinning drug warfarin
- taking sedatives or tranquilizers (nighttime only)

When using this product

- do not exceed recommended dosage
- excitability may occur, especially in children (nighttime only)
- marked drowsiness may occur (nighttime only)
- alcohol, sedatives, and tranquilizers may increase drowsiness (nighttime only)
- use caution when driving a motor vehicle or operating machinery (nighttime only)
- avoid alcoholic beverages (nighttime only)

Stop use and ask a doctor if

- nervousness, dizziness, or sleeplessness occur
- pain, nasal congestion, or cough gets worse or lasts more than 7 days
- new symptoms occur
- fever gets worse or lasts more than 3 days
- redness or swelling is present
- cough comes back or occurs with rash or headache that lasts. These could be signs of a serious condition.

If pregnant or breast-feeding,

ask a health professional before use.

Keep out of reach of children.

In case of overdose, get medical help or contact a Poison Control Center right away. Prompt medical attention is critical for adults as well as for children even if you do not notice any signs or symptoms.

Do not take DAYTIME and NIGHTTIME products at the same time.

Directions

- do not take more than directed
- do not take more than 12 caplets in any 24-hour period
- adults and children 12 years and over: take 2 caplets every 4 hours
- children under 12 years: do not use

Other information

- each caplet contains: sodium 3 mg (daytime only)
- TAMPER EVIDENT: DO NOT USE IF OUTER PACKAGE IS OPENED OR BLISTER IS TORN OR BROKEN
- store at 25°C (77°F); excursions permitted between 15°-30°C (59°-86°F)
- see end flap for expiration date and lot number

Inactive ingredients (daytime only)

corn starch, crospovidone, FD&C red #40 aluminum lake, FD&C yellow #6 aluminum lake, magnesium stearate, maltodextrin, microcrystalline cellulose, polyethylene glycol, polyvinyl alcohol, povidone, silicon dioxide, sodium starch glycolate, stearic acid, talc, titanium dioxide

Inactive ingredients (nighttime only)

corn starch, croscarmellose sodium, crospovidone, FD&C blue #1 aluminum lake, FD&C blue #2 aluminum lake, iron oxide yellow, magnesium stearate, methacrylic acid and ethyl acrylate copolymer, microcrystalline cellulose, polyethylene glycol, polyvinyl alcohol, povidone, silicon dioxide, sodium bicarbonate, stearic acid, talc, titanium dioxide

Questions or comments?

1-800-426-9391

Principal display panel

DAY & NIGHT PACK

• WALGREENS •
PHARMACIST RECOMMENDED†
Walgreens

DAYTIME
Sinus
Pressure
& Pain

ACETAMINOPHEN
PAIN RELIEVER
GUAIFENESIN
EXPECTORANT
PHENYLEPHRINE HCl
NASAL DECONGESTANT

Maximum Strength

24 CAPLETS

ACTUAL SIZE

NIGHTTIME
Sinus
Pressure
& Pain

ACETAMINOPHEN
PAIN RELIEVER
DIPHENHYDRAMINE HCl
ANTIHISTAMINE
COUGH SUPPRESSANT
PHENYLEPHRINE HCl
NASAL DECONGESTANT

Maximum Strength

16 CAPLETS

ACTUAL SIZE

TOTAL 40 CAPLETS

TAMPER EVIDENT: DO NOT USE IF PACKAGE IS OPENED OR IF BLISTER UNIT IS TORN,
BROKEN OR SHOWS ANY SIGNS OF TAMPERING

Do Not Take Daytime
and Nighttime Products
at the Same Time.

†Our pharmacists recommend the Walgreens brand.
We invite you to compare to national brands.

50844 REV0824B61569410

DISTRIBUTED BY: WALGREEN CO.
DEERFIELD, IL 60015
100% SATISFACTION GUARANTEED
walgreens.com
©2025 Walgreen Co.

NDC 0363-6156-10

Walgreens 44-615694